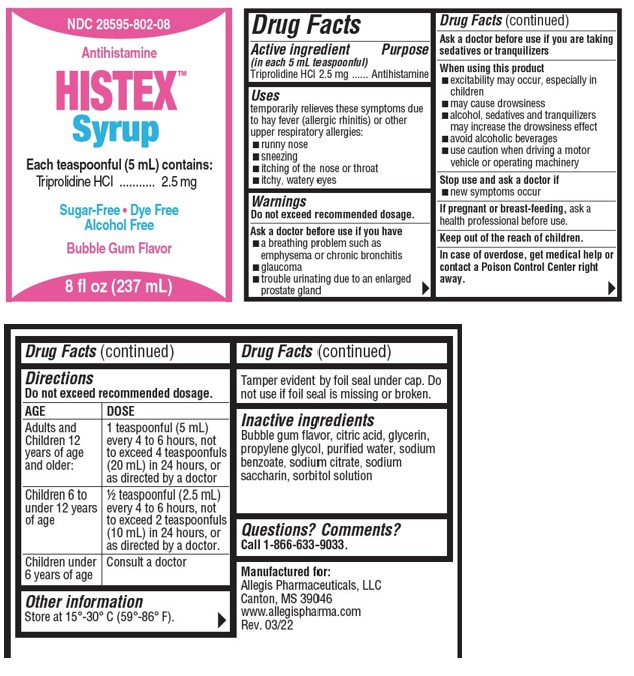 DRUG LABEL: HISTEX
NDC: 28595-802 | Form: SYRUP
Manufacturer: Allegis Pharmaceuticals, LLC
Category: otc | Type: HUMAN OTC DRUG LABEL
Date: 20240108

ACTIVE INGREDIENTS: TRIPROLIDINE HYDROCHLORIDE 2.5 mg/5 mL
INACTIVE INGREDIENTS: SODIUM BENZOATE; CITRIC ACID MONOHYDRATE; GLYCERIN; PROPYLENE GLYCOL; WATER; SODIUM CITRATE, UNSPECIFIED FORM; SACCHARIN SODIUM; SORBITOL

HISTEX™ Syrup

Drug Facts

Active ingredients (in each 5 mL teaspoonful)

Triprolidine HCl 2.5 mg

Purpose

Antihistamine

Uses

temporarily relieves these symptoms due to hay fever (allergic rhinitis) or other upper respiratory allergies:

- runny nose
- sneezing
- itching of the nose or throat
- itchy, watery eyes

Warnings

Do not exceed recommended dosage.

Ask a doctor before use if you have

- a breathing problem such as emphysema or chronic bronchitis
- glaucoma
- trouble urinating due to an enlarged prostate gland

Ask a doctor before use if you are taking sedatives or tranquilizers

When using this product

- excitability may occur, especially in children
- may cause drowsiness
- alcohol, sedatives and tranquilizers may increase the drowsiness effect
- avoid alcoholic beverages
- use caution when driving a motor vehicle or operating machinery

Stop use and ask a doctor if

- new symptoms occur

PREGNANCY OR BREAST FEEDING

If pregnant or breast-feeding, ask a health professional before use.

Keep out of the reach of children.

In case of overdose, get medical help or contact a Poison Control Center right away.

Directions

Do not exceed recommended dosage.

AGE | DOSE
Adults and Childen 12 years of age and older: | 1 teaspoonful (5 mL) every 4 to 6 hours, not to exceed 4 teaspoonfuls (20 mL) in 24 hours, or as directed by a doctor
Childen 6 to under 12 years of age | ½ teaspoonful (2.5 mL) every 4 to 6 hours, not to exceed 2 teaspoonfuls (10 mL) in 24 hours, or as directed by a doctor.
Children under 6 years of age | Consult a doctor

Other Information

Store at 15°-30° C (59°-86° F).

Tamper evident by foil seal under cap. Do not use if foil seal is missing or broken.

Dispense in a tight, light-resistant container with a child-resistant cap.

Inactive ingredients

Citric Acid, Glycerin, Propylene Glycol, Purified Water, Sodium Citrate, Sodium Saccharin, Sorbitol, Bubble Gum Flavor.

Questions? Comments?

Call 1-866-633-9033.

PRINCIPAL DISPLAY PANEL - 237 mL Bottle Label

NDC 28595-802-08

Antihistamine

HISTEX™
Syrup

Each teaspoonful (5 mL)
contains:
Triprolidine HCl 2.5 mg

Sugar-Free • Dye Free
Alcohol Free

Bubble Gum Flavor

8 fl oz (237 mL)